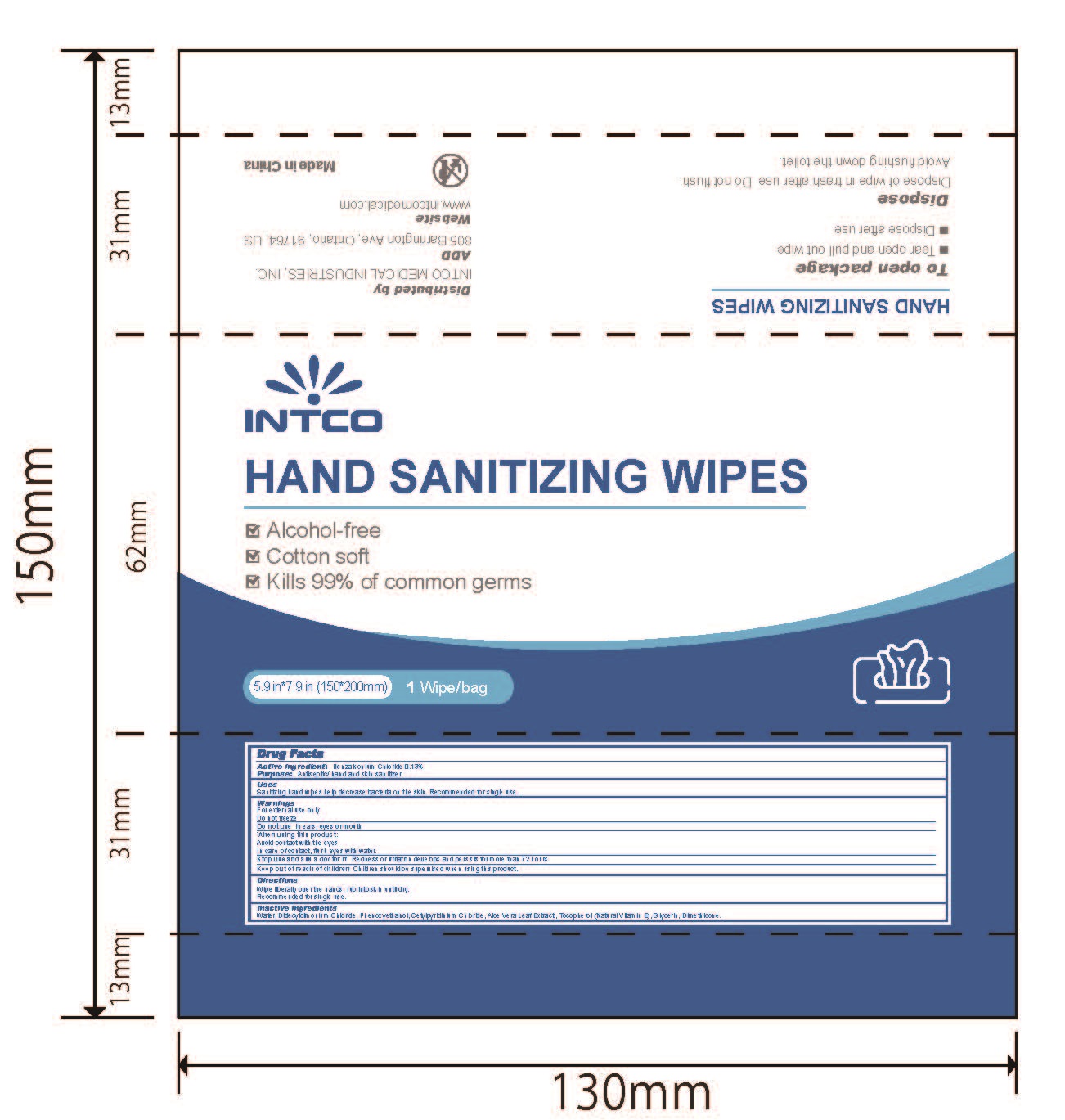 DRUG LABEL: INTCO HAND SANITIZING WIPES
NDC: 74201-001 | Form: CLOTH
Manufacturer: Jiangsu Intco Medical Products Co., Ltd
Category: otc | Type: HUMAN OTC DRUG LABEL
Date: 20210312

ACTIVE INGREDIENTS: BENZALKONIUM CHLORIDE 0.13 1/100 1
INACTIVE INGREDIENTS: CETYLPYRIDINIUM CHLORIDE; DIMETHICONE; GLYCERIN; DIDECYLDIMONIUM CHLORIDE; WATER; TOCOPHEROL; PHENOXYETHANOL; ALOE VERA LEAF

INTCO HAND SANITIZING WIPES
1 WIPE

Active ingredient:

Benzalkonium Chloride 0.13%

Purpose

Antiseptic/ hand and skin sanitizer

Uses

Sanitizing hand wipes help decrease bacteria on the skin. Recommended for single use.

Warnings

For external use only

Do not freeze

Do not use

In ears, eyes or mouth

When using this product:

Avoid contact with the eyes

In case of contact, flush eyes with water.

Stop use and ask a doctor if

Redness or irritation develops and persists for more than 72 hours.

Keep out of reach of children

Children should be supervised when using this product.

Directions

Wipe liberally over the hands, rub into skin until dry.

Recommended for single use.

Inactive ingredients

Water, Didecyldimonium Chloride, Phenoxyethanol, Cetylpyridinium Chloride, Aloe Vera Leaf Extract , Tocopherol (Natural Vitamin E), Glycerin, Dimethicone.

INSTRUCTIONS FOR USE

To open package

- Tear open and pull out wipe
- Dispose after use

Dispose

Dispose of wipe in trash after use. Do not flush.

Avoid flushing down the toilet.